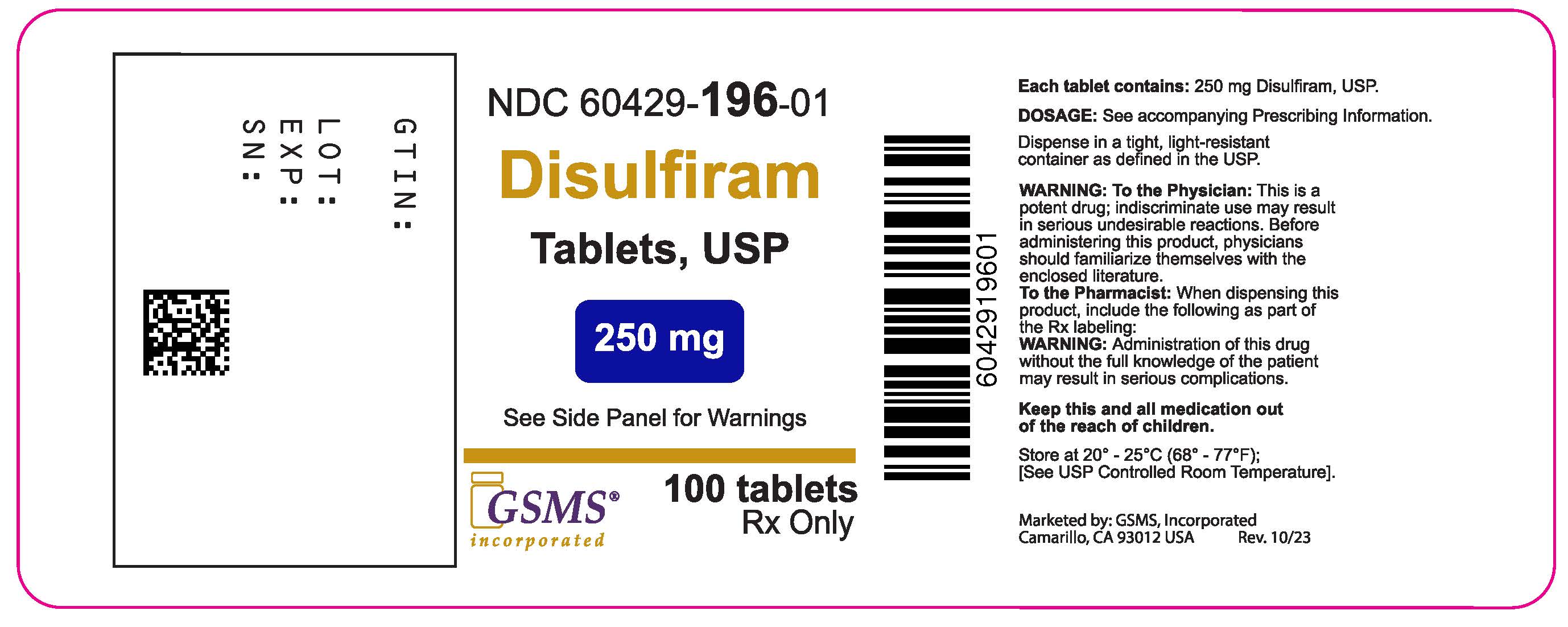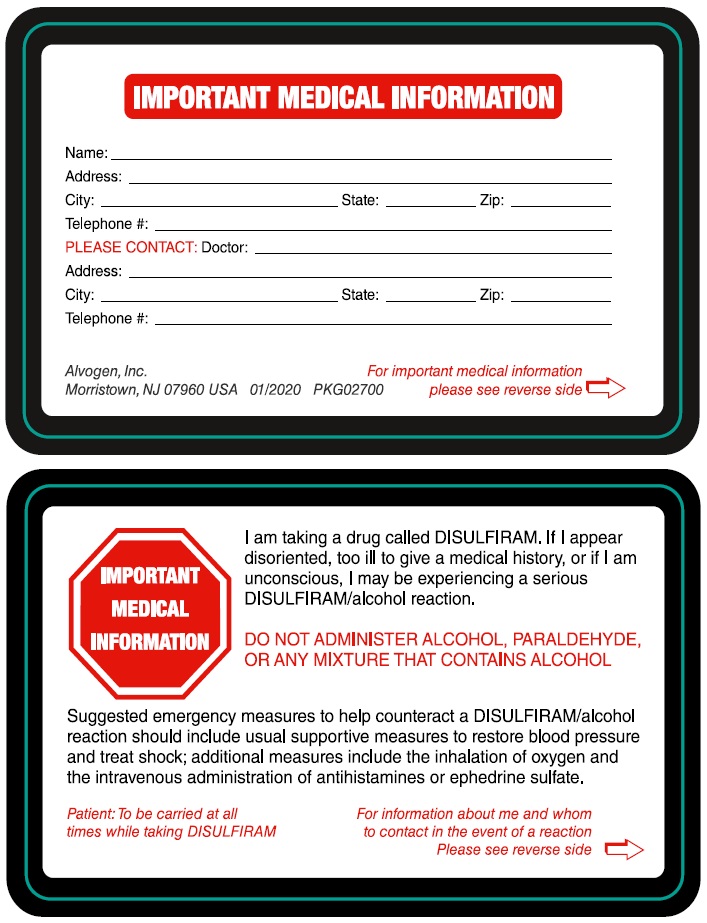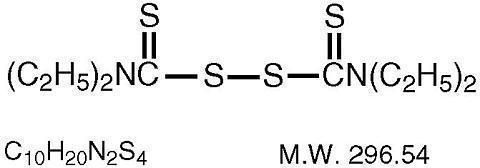 DRUG LABEL: Disulfiram
NDC: 60429-196 | Form: TABLET
Manufacturer: Golden State Medical Supply, Inc.
Category: prescription | Type: HUMAN PRESCRIPTION DRUG LABEL
Date: 20251211

ACTIVE INGREDIENTS: DISULFIRAM 250 mg/1 1
INACTIVE INGREDIENTS: ANHYDROUS LACTOSE; MAGNESIUM STEARATE; SILICON DIOXIDE; MICROCRYSTALLINE CELLULOSE; SODIUM STARCH GLYCOLATE TYPE A POTATO; STEARIC ACID

Disulfiram Tablets, USP
IN ALCOHOLISM
Rx only

WARNING

Disulfiram should neverbe administered to a patient when he is in a state of alcohol intoxication, or without his full knowledge.
The physician should instruct relatives accordingly.

DESCRIPTION

Disulfiram is an alcohol antagonist drug.

CHEMICAL NAME:

bis(diethylthiocarbamoyl) disulfide.

STRUCTURAL FORMULA:

Disulfiram occurs as a white to off-white, odorless, and almost tasteless powder, soluble in water to the extent of about 20 mg in 100 mL, and in alcohol to the extent of about 3.8 g in 100 mL.

Each tablet for oral administration contains 250 mg disulfiram, USP. Tablets also contain colloidal silicon dioxide, anhydrous lactose, magnesium stearate, microcrystalline cellulose, sodium starch glycolate, and stearic acid.

CLINICAL PHARMACOLOGY

Disulfiram produces a sensitivity to alcohol which results in a highly unpleasant reaction when the patient under treatment ingests even small amounts of alcohol.

Disulfiram blocks the oxidation of alcohol at the acetaldehyde stage. During alcohol metabolism following disulfiram intake, the concentration of acetaldehyde occurring in the blood may be 5 to 10 times higher than that found during metabolism of the same amount of alcohol alone.

Accumulation of acetaldehyde in the blood produces a complex of highly unpleasant symptoms referred to hereinafter as the disulfiram-alcohol reaction. This reaction, which is proportional to the dosage of both disulfiram and alcohol, will persist as long as alcohol is being metabolized. Disulfiram does not appear to influence the rate of alcohol elimination from the body.

Disulfiram is absorbed slowly from the gastrointestinal tract and is eliminated slowly from the body. One (or even two) weeks after a patient has taken his last dose of disulfiram, ingestion of alcohol may produce unpleasant symptoms.

Prolonged administration of disulfiram does not produce tolerance; the longer a patient remains on therapy, the more exquisitely sensitive he becomes to alcohol.

INDICATIONS AND USAGE

Disulfiram is an aid in the management of selected chronic alcohol patients who wantto remain in a state of enforced sobriety so that supportive and psychotherapeutic treatment may be applied to best advantage.

Disulfiram is not a cure for alcoholism. When used alone, without proper motivation and supportive therapy, it is unlikely that it will have any substantive effect on the drinking pattern of the chronic alcoholic.

CONTRAINDICATIONS

Patients who are receiving or have recently received metronidazole, paraldehyde, alcohol, or alcohol-containing preparations, e.g., cough syrups, tonics and the like, should not be given disulfiram.

Disulfiram is contraindicated in the presence of severe myocardial disease or coronary occlusion, psychoses, and hypersensitivity to disulfiram or to other thiuram derivatives used in pesticides and rubber vulcanization.

WARNINGS

Disulfiram should neverbe administered to a patient when he is in a state of alcohol intoxication, or without his full knowledge.
The physician should instruct relatives accordingly.

The patient must be fully informed of the disulfiram-alcohol reaction. He must be strongly cautioned against surreptitious drinking while taking the drug, and he must be fully aware of the possible consequences. He should be warned to avoid alcohol in disguised forms, i.e., in sauces, vinegars, cough mixtures, and even in aftershave lotions and back rubs. He should also be warned that reactions may occur with alcohol up to 14 days after ingesting disulfiram.

The Disulfiram-Alcohol Reaction

Disulfiram plus alcohol, even small amounts, produce flushing, throbbing in head and neck, throbbing headache, respiratory difficulty, nausea, copious vomiting, sweating, thirst, chest pain, palpitation, dyspnea, hyperventilation, tachycardia, hypotension, syncope, marked uneasiness, weakness, vertigo, blurred vision, and confusion. In severe reactions there may be respiratory depression, cardiovascular collapse, arrhythmias, myocardial infarction, acute congestive heart failure, unconsciousness, convulsions, and death.

The intensity of the reaction varies with each individual, but is generally proportional to the amounts of disulfiram and alcohol ingested. Mild reactions may occur in the sensitive individual when the blood alcohol concentration is increased to as little as 5 mg to 10 mg per 100 mL. Symptoms are fully developed at 50 mg per 100 mL, and unconsciousness usually results when the blood alcohol level reaches 125 mg to 150 mg.

The duration of the reaction varies from 30 to 60 minutes, to several hours in the more severe cases, or as long as there is alcohol in the blood.

Concomitant Conditions

Because of the possibility of an accidental disulfiram-alcohol reaction, disulfiram should be used with extreme caution in patients with any of the following conditions: diabetes mellitus, hypothyroidism, epilepsy, cerebral damage, chronic and acute nephritis, hepatic cirrhosis or insufficiency.

PRECAUTIONS

Patients with a history of rubber contact dermatitis should be evaluated for hypersensitivity to thiuram derivatives before receiving disulfiram (see CONTRAINDICATIONS).

It is suggested that every patient under treatment carry an Identification Cardstating that he is receiving disulfiram and describing the symptoms most likely to occur as a result of the disulfiram-alcohol reaction. In addition, this card should indicate the physician or institution to be contacted in an emergency. (Cards may be obtained from Alvogen, Inc. upon request.)

Alcoholism may accompany or be followed by dependence on narcotics or sedatives. Barbiturates and disulfiram have been administered concurrently without untoward effects; the possibility of initiating a new abuse should be considered.

Hepatic toxicity including hepatic failure resulting in transplantation or death have been reported. Severe and sometimes fatal hepatitis associated with disulfiram therapy may develop even after many months of therapy. Hepatic toxicity has occurred in patients with or without prior history of abnormal liver function. Patients should be advised to immediately notify their physician of any early symptoms of hepatitis, such as fatigue, weakness, malaise, anorexia, nausea, vomiting, jaundice, or dark urine.

Baseline and follow-up liver function tests (10 to 14 days) are suggested to detect any hepatic dysfunction that may result with disulfiram therapy. In addition, a complete blood count and serum chemistries, including liver function tests, should be monitored.

Patients taking disulfiram tablets should not be exposed to ethylene dibromide or its vapors. This precaution is based on preliminary results of animal research currently in progress that suggest a toxic interaction between inhaled ethylene dibromide and ingested disulfiram resulting in a higher incidence of tumors and mortality in rats. A correlation between this finding and humans, however, has not been demonstrated.

Drug Interactions

Disulfiram appears to decrease the rate at which certain drugs are metabolized and therefore may increase the blood levels and the possibility of clinical toxicity of drugs given concomitantly.

DISULFIRAM SHOULD BE USED WITH CAUTION IN THOSE PATIENTS RECEIVING PHENYTOIN AND ITS CONGENERS, SINCE THE CONCOMITANT ADMINISTRATION OF THESE TWO DRUGS CAN LEAD TO PHENYTOIN INTOXICATION. PRIOR TO ADMINISTERING DISULFIRAM TO A PATIENT ON PHENYTOIN THERAPY, A BASELINE PHENYTOIN SERUM LEVEL SHOULD BE OBTAINED. SUBSEQUENT TO INITIATION OF DISULFIRAM THERAPY, SERUM LEVELS OF PHENYTOIN SHOULD BE DETERMINED ON DIFFERENT DAYS FOR EVIDENCE OF AN INCREASE OR FOR A CONTINUING RISE IN LEVELS. INCREASED PHENYTOIN LEVELS SHOULD BE TREATED WITH APPROPRIATE DOSAGE ADJUSTMENT.

It may be necessary to adjust the dosage of oral anticoagulants upon beginning or stopping disulfiram, since disulfiram may prolong prothrombin time.

Patients taking isoniazid when disulfiram is given should be observed for the appearance of unsteady gait or marked changes in mental status, the disulfiram should be discontinued if such signs appear.

In rats, simultaneous ingestion of disulfiram and nitrite in the diet for 78 weeks has been reported to cause tumors, and it has been suggested that disulfiram may react with nitrites in the rat stomach to form a nitrosamine, which is tumorigenic. Disulfiram alone in the rat's diet did not lead to such tumors. The relevance of this finding to humans is not known at this time.

Usage In Pregnancy

The safe use of this drug in pregnancy has not been established. Therefore, disulfiram should be used during pregnancy only when, in the judgement of the physician, the probable benefits outweigh the possible risks.

Pediatric Use

Safety and effectiveness in pediatric patients have not been established.

Nursing Mothers

It is not known whether this drug is excreted in human milk. Since many drugs are so excreted, disulfiram should not be given to nursing mothers.

Geriatric Use

A determination has not been made whether controlled clinical studies of disulfiram included sufficient numbers of subjects aged 65 and over to define a difference in response from younger subjects. Other reported clinical experience has not identified differences in responses between the elderly and younger patients. In general, dose selection for an elderly patient should be cautious, usually starting at the low end of the dosing range, reflecting the greater frequency of decreased hepatic, renal or cardiac function, and of concomitant disease or other drug therapy.

ADVERSE REACTIONS

(See CONTRAINDICATIONS, WARNINGS, and PRECAUTIONS.)

OPTIC NEURITIS, PERIPHERAL NEURITIS, POLYNEURITIS, AND PERIPHERAL NEUROPATHY MAY OCCUR FOLLOWING ADMINISTRATION OF DISULFIRAM.

Multiple cases of hepatitis, including both cholestatic and fulminant hepatitis, as well as hepatic failure resulting in transplantation or death, have been reported with administration of disulfiram.

Occasional skin eruptions are, as a rule, readily controlled by concomitant administration of an antihistaminic drug.

In a small number of patients, a transient mild drowsiness, fatigability, impotence, headache, acneform eruptions, allergic dermatitis, or a metallic or garlic-like aftertaste may be experienced during the first two weeks of therapy. These complaints usually disappear spontaneously with the continuation of therapy, or with reduced dosage.

Psychotic reactions have been noted, attributable in most cases to high dosage, combined toxicity (with metronidazole or isoniazid), or to the unmasking of underlying psychoses in patients stressed by the withdrawal of alcohol.

To report SUSPECTED ADVERSE REACTIONS, contact Alvogen, Inc. at 1-866-770-3024 or FDA at 1-800-FDA-1088 or www.fda.gov/medwatch.

OVERDOSAGE

No specific information is available on the treatment of overdosage with disulfiram. It is recommended that the physician contact the local Poison Control Center.

DOSAGE AND ADMINISTRATION

Disulfiram should never be administered until the patient has abstained from alcohol for at least 12 hours.

Initial Dosage Schedule

In the first phase of treatment, a maximumof 500 mg daily is given in a single dose for one to two weeks. Although usually taken in the morning, disulfiram may be taken on retiring by patients who experience a sedative effect. Alternatively, to minimize, or eliminate, the sedative effect, dosage may be adjusted downward.

Maintenance Regimen

The average maintenance dose is 250 mg daily (range, 125 mg to 500 mg), it should not exceed 500 mg daily.

Note: Occasionally patients, while seemingly on adequate maintenance doses of disulfiram, report that they are able to drink alcoholic beverages with impunity and without any symptomatology. All appearances to the contrary, such patients must be presumed to be disposing of their tablets in some manner without actually taking them. Until such patients have been observed reliably taking their daily disulfiram tablets (preferably crushed and well mixed with liquid), it cannot be concluded that disulfiram is ineffective.

Duration of Therapy

The daily, uninterrupted administration of disulfiram must be continued until the patient is fully recovered socially and a basis for permanent self-control is established. Depending on the individual patient, maintenance therapy may be required for months or even years.

Trial with Alcohol

During early experience with disulfiram, it was thought advisable for each patient to have at least one supervised alcohol-drug reaction. More recently, the test reaction has been largely abandoned. Furthermore, such a test reaction should never be administered to a patient over 50 years of age. A clear, detailed and convincing description of the reaction is felt to be sufficient in most cases.

However, where a test reaction is deemed necessary, the suggested procedure is as follows:
After the first one to two weeks' therapy with 500 mg daily, a drink of 15 mL (1/2 oz) of 100 proof whiskey, or equivalent, is taken slowly. This test dose of alcoholic beverage may be repeated once only, so that the total dose does not exceed 30 mL (1 oz) of whiskey. Once a reaction develops, no more alcohol should be consumed. Such tests should be carried out only when the patient is hospitalized, or comparable supervision and facilities, including oxygen, are available.

Management of Disulfiram-Alcohol Reaction

In severe reactions, whether caused by an excessive test dose or by the patient's unsupervised ingestion of alcohol, supportive measures to restore blood pressure and treat shock should be instituted. Other recommendations include: oxygen, carbogen (95% oxygen and 5% carbon dioxide), vitamin C intravenously in massive doses (1 g) and ephedrine sulfate. Antihistamines have also been used intravenously. Potassium levels should be monitored, particularly in patients on digitalis, since hypokalemia has been reported.

HOW SUPPLIED

Disulfiram Tablets, USP are white, round, unscored tablets debossed 607.

Bottle of 30 NDC 60429-196-30

Bottle of 100 NDC 60429-196-01

Dispense in a tight, light-resistant container as defined in the USP.

Store at 20°C to 25°C (68°F to 77°F). [See USP Controlled Room Temperature].

Manufactured by:
Norwich Pharmaceuticals, Inc.
Norwich, NY 13815 USA

Distributed by:
Alvogen, Inc.
Morristown, NJ 07960 USA

PI607-03
Rev. 01/2020
PKG02698

Marketed by:

GSMS, Inc.

Camarillo, CA 93012 USA

PACKAGE LABEL

NDC60429-196-01

DISULFIRAM TABLETS, USP
250 mg

WARNING: To the Physician:This is a potent drug; indiscriminate use may result in serious undesirable reactions.
Before administering this product, physicians should familiarize themselves with the enclosed literature.

To the Pharmacist:When dispensing this product, include the following as part of the Rx labeling:
WARNING:Administration of this drug without the full knowledge of the patient may result in serious complications.

30 Tablets
Rx only